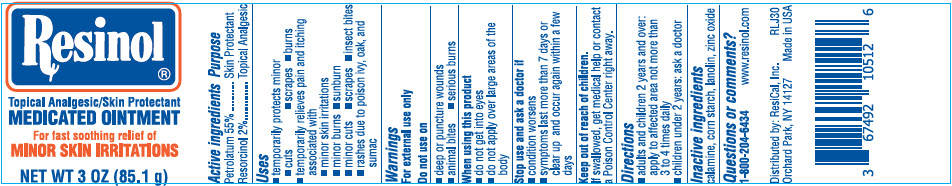 DRUG LABEL: Resinol
NDC: 67492-105 | Form: OINTMENT
Manufacturer: ResiCal, Inc.
Category: otc | Type: HUMAN OTC DRUG LABEL
Date: 20251217

ACTIVE INGREDIENTS: PETROLATUM 55 g/100 g; RESORCINOL 2 g/100 g
INACTIVE INGREDIENTS: STARCH, CORN; LANOLIN; ZINC OXIDE; FERRIC OXIDE RED

Resinol®

Active ingredients

Petrolatum 55%, Resorcinol 2%

Uses

PURPOSE

- temporarily protects minor
  - cuts
  - scrapes
  - burns
- temporarily relieves pain and itching associated with
  - minor skin irritations
  - minor burns
  - sunburn
  - minor cuts
  - scrapes
  - insect bites
  - rashes due to poison ivy, oak, and sumac

Warnings

For external use only

Do not use on

- deep or puncture wounds
- animal bites
- serious burns

When using this product

- do not get into eyes
- do not apply over large areas of the body

Stop use and ask a doctor if

- condition worsens
- symptoms last more than 7 days or clear up and occur again within a few days

Keep out of reach of children.

If swallowed, get medical help or contact a Poison Control Center right away.

Directions

- adults and children 2 years and over: apply to affected area not more than 3 to 4 times daily
- children under 2 years: ask a doctor

Inactive ingredients

calamine, corn starch, lanolin, zinc oxide

Questions or comments?

1-800-204-6434 www.resinol.com

Distributed by: ResiCal, Inc.
Orchard Park, NY 14127

PRINCIPAL DISPLAY PANEL - 85.1 g Jar Label

Resinol®

Topical Analgesic/Skin Protectant
MEDICATED OINTMENT

For fast soothing relief of
MINOR SKIN IRRITATIONS

NET WT 3 OZ (85.1 g)